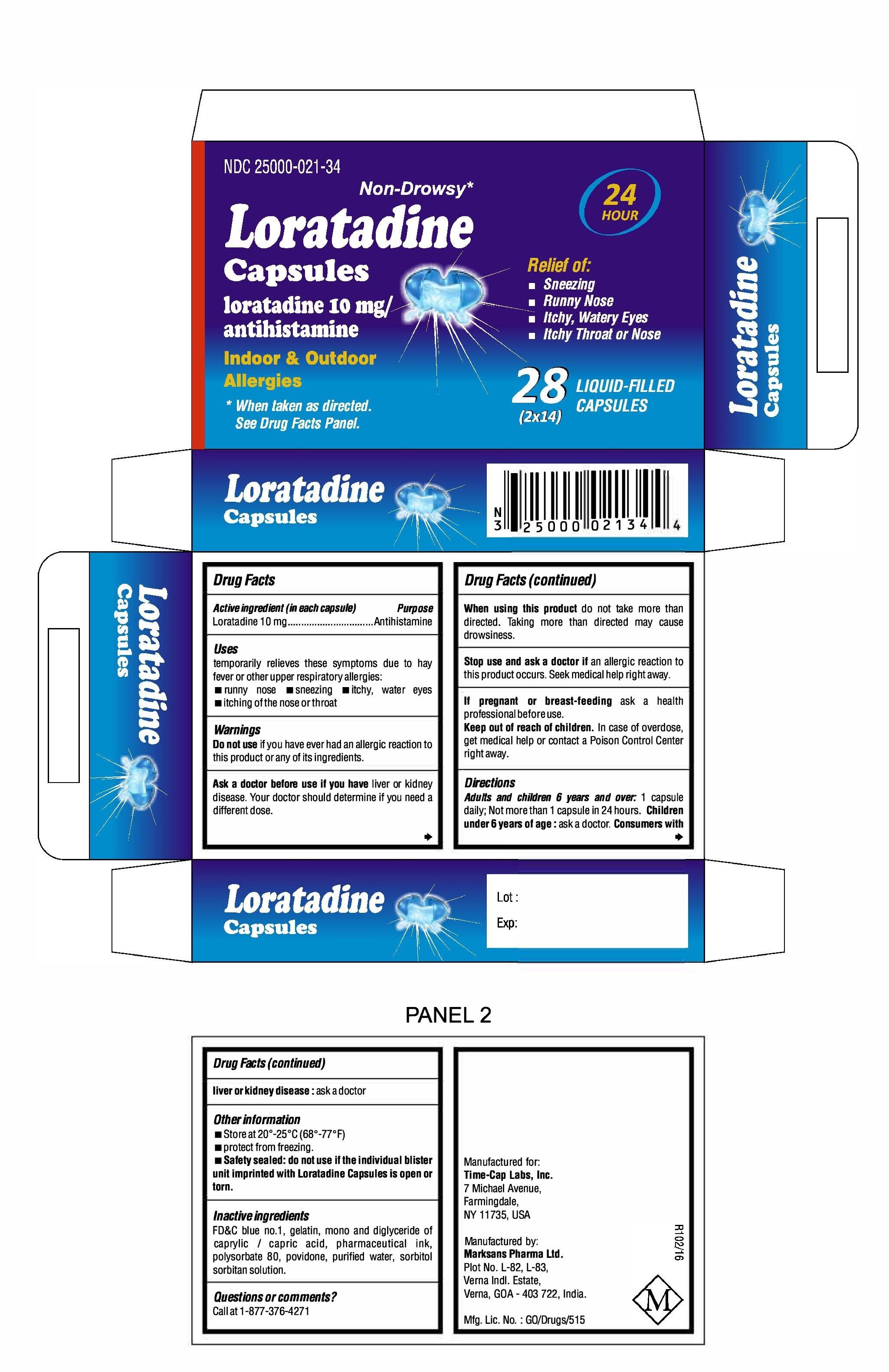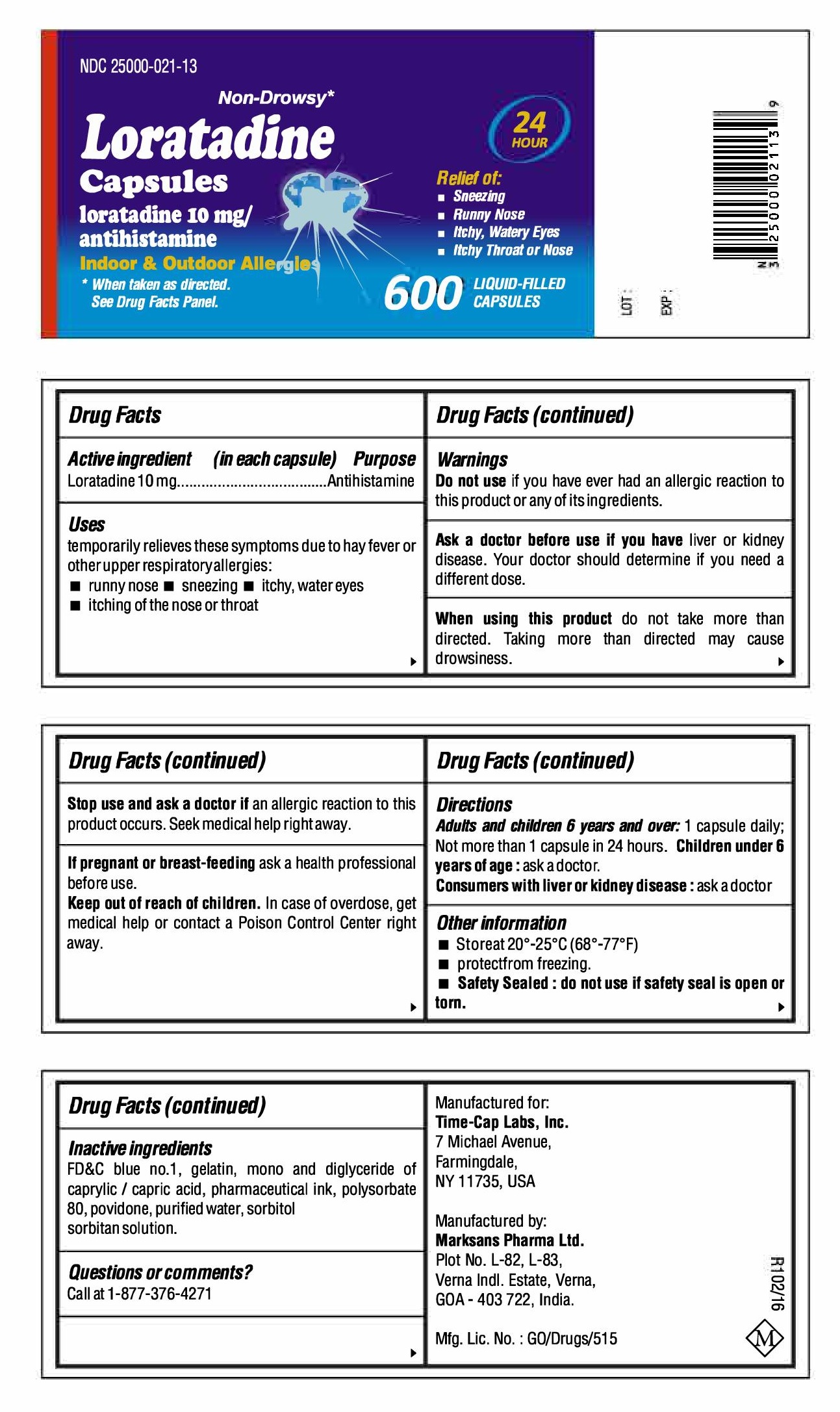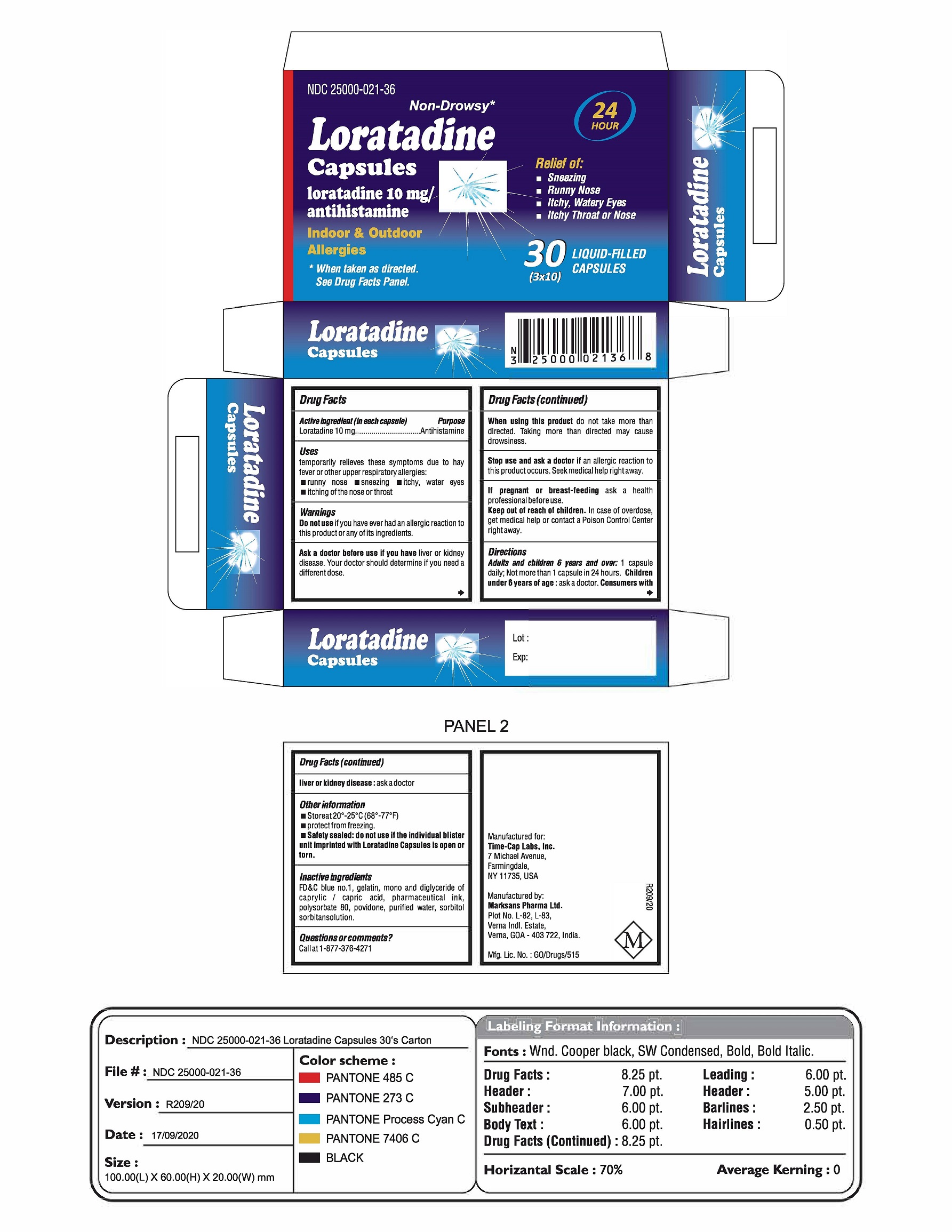 DRUG LABEL: Loratadine
NDC: 25000-021 | Form: CAPSULE, LIQUID FILLED
Manufacturer: MARKSANS PHARMA LIMITED
Category: otc | Type: Human OTC Drug Label
Date: 20211115

ACTIVE INGREDIENTS: LORATADINE 10 mg/1 1
INACTIVE INGREDIENTS: FD&C BLUE NO. 1; GELATIN; CAPRIC ACID; POVIDONE K30; WATER; SORBITOL; POLYSORBATE 80; SORBITAN

Loratadine Liquid Filled Capsules, 10 mg (OTC)
Drug Facts

Active ingredient (in each capsule)

Loratadine 10mg

Purpose

Antihistamine

Uses

temporarily relieves these symptoms due to hay fever or other upper respiratory allergies:

• runny nose

• itchy, watery eyes

• sneezing

• itching of the nose or throat

WARNINGS

Do not use

if you have ever had an allergic reaction to this product or any of its ingredients.

Ask a doctor before use if you have

you have liver or kidney disease. Your doctor should determine if you need a different dose.

When using this product

do not take more than directed. Taking more than directed may cause drowsiness.

Stop use and ask a doctor if

an allergic reaction to this product occurs. Seek medical help right away.

If pregnant or breast-feeding

ask a health professional before use.

Keep out of reach of children.

In case of overdose, get medical help or contact a Poison Control Center right away.

Directions

Adults and children 6 years and over: 1 capsule daily; Not more than 1 capsule in 24 hours.
Children under 6 years of age: ask a doctor.
Consumers with liver or kidney disease: ask a doctor.

Inactive ingredients

FD&C blue no. 1, gelatin, mono and diglyceride of caprylic/capric acid, pharmaceutical ink, polysorbate 80, povidone, purified water, sorbitol sorbitan solution.
Questions or comments?
Call at 1-877-376-4271

Other information

- Store at 20°-25°C (68°-77°F)
- protect from freezing.
- Safety sealed: do not use if the individual blister unit imprinted with Loratadine Capsules is open or torn.

Manufactured for

Time-Cap Labs. Inc.
7 Michael Avenue,
Farmingdale,
NY 11735, USA

Manufactured by

Marksans Pharma Ltd.
Plot No. L-82, L-83,
Verna Indl. Estate,
Verna, GOA 403722, India.

Principal Display Panel

NDC# 25000-021-13
Loratadine Capsules, 10 mg
600 counts Bottle Label

NDC# 25000-021-34
Loratadine Capsules, 10 mg
28 counts Blister Pack

PRINCIPAL DISPLAY PANEL

NDC# 25000-021-36
Loratadine Capsules, 10 mg
3x10 carton Label